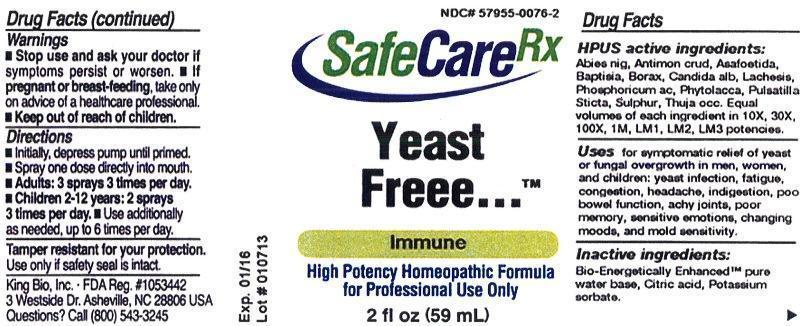 DRUG LABEL: Yeast Freee
NDC: 57955-0076 | Form: LIQUID
Manufacturer: King Bio Inc.
Category: homeopathic | Type: HUMAN PRESCRIPTION DRUG LABEL
Date: 20130227

ACTIVE INGREDIENTS: PICEA MARIANA RESIN 10 [hp_X]/59 mL; ANTIMONY TRISULFIDE 10 [hp_X]/59 mL; ASAFETIDA 10 [hp_X]/59 mL; BAPTISIA TINCTORIA ROOT 10 [hp_X]/59 mL; SODIUM BORATE 10 [hp_X]/59 mL; CANDIDA ALBICANS 10 [hp_X]/59 mL; LACHESIS MUTA VENOM 10 [hp_X]/59 mL; PHOSPHORIC ACID 10 [hp_X]/59 mL; PHYTOLACCA AMERICANA ROOT 10 [hp_X]/59 mL; PULSATILLA VULGARIS 10 [hp_X]/59 mL; LOBARIA PULMONARIA 10 [hp_X]/59 mL; SULFUR 10 [hp_X]/59 mL; THUJA OCCIDENTALIS LEAFY TWIG 10 [hp_X]/59 mL
INACTIVE INGREDIENTS: WATER; CITRIC ACID MONOHYDRATE; POTASSIUM SORBATE

Yeast Freee

Active Ingredients

HPUS active ingredients: Abies nigra, Antimonium crudum, Asafoetida, Baptisia tinctoria, Borax, Candida albicans, Lachesis mutus, Phosphoricum acidum, Phytolacca decandra, Pulsatilla, Sticta Plumonaria, Sulphur, Thuja occidentalis.

Equal volumes of each ingredient in 10X, 30X, 100X, 1M, LM1, LM2, LM3 potencies.

Inactive Ingredients

Bio-Energetically Enhanced™ pure water base, Citric acid, Potassium sorbate.

Purpose

Uses for symptomatic relief of yeast or fungal overgrowth in men, women, and children:

- Yeast infection
- fatigue
- congestion
- headache
- indigestion
- poor bowel function
- achy joints
- poor memory
- sensitive emotions
- changing moods and mold sensitivity

Warnings

- Stop use and ask your doctor if symptoms persist or worsen.
- If pregnant or breast-feeding, take only on advice of a healthcare professional.
- Keep out of reach of children.

Tamper resistant for your protection. Use only if safety seal is intact

Keep out of reach of children.

Indications and Usage

Use for symptomatic relief of yeast or fungal overgrowth in men, women, and children: yeast infection, fatigue, congestion, headache, indigestion, poor bowel function, achy joints, poor memory, sensitive emotions, changing moods, and mold sensitivity.